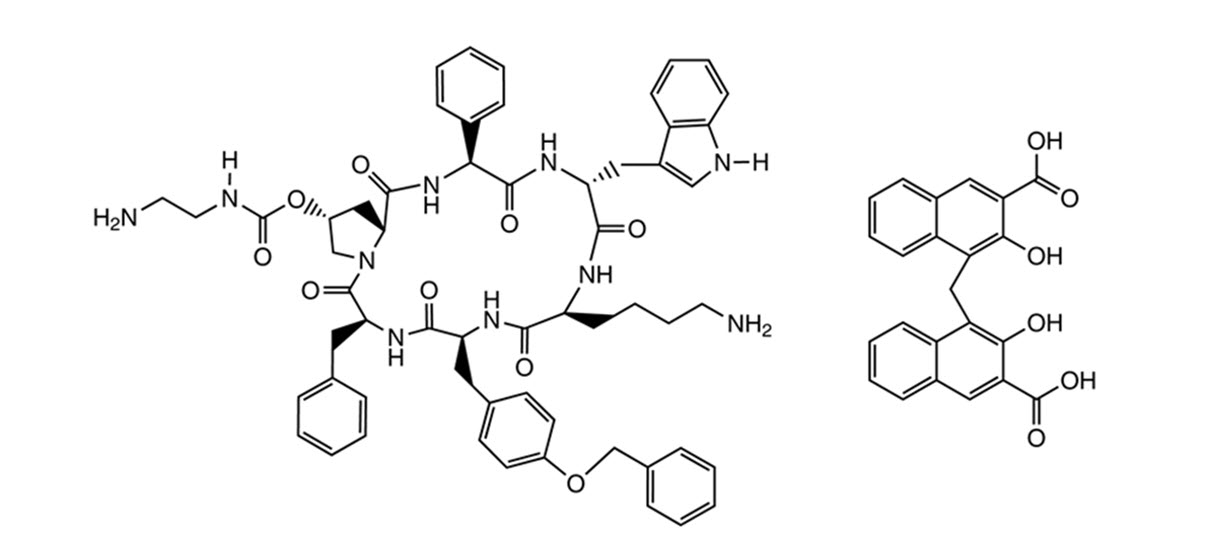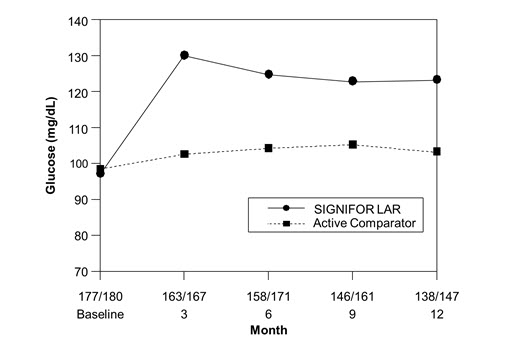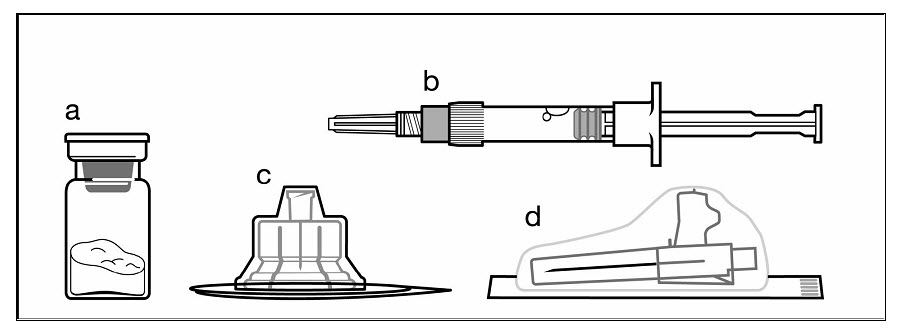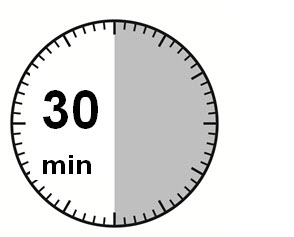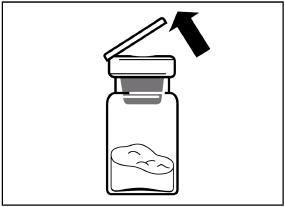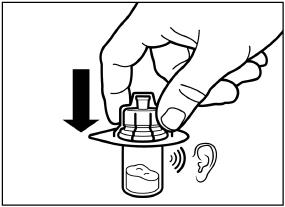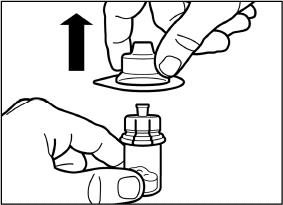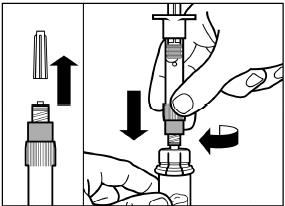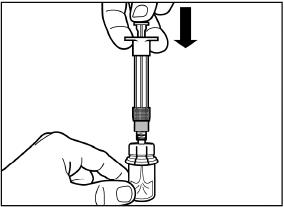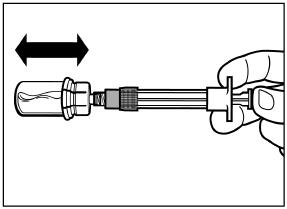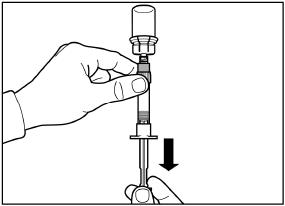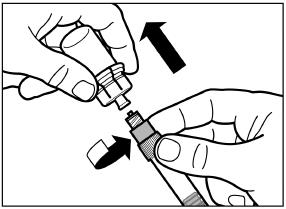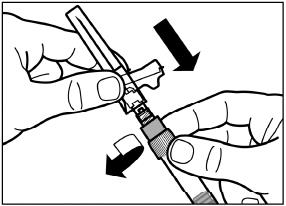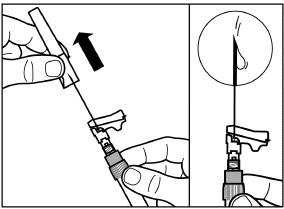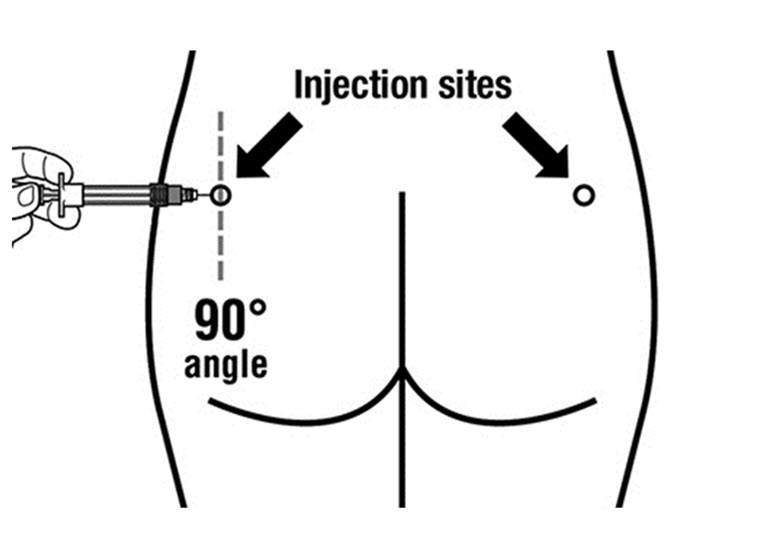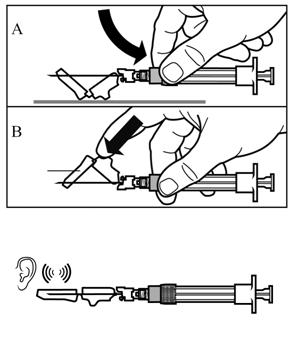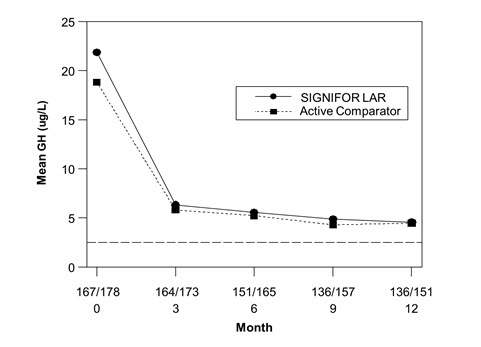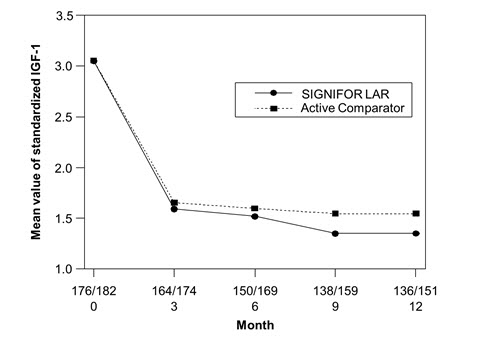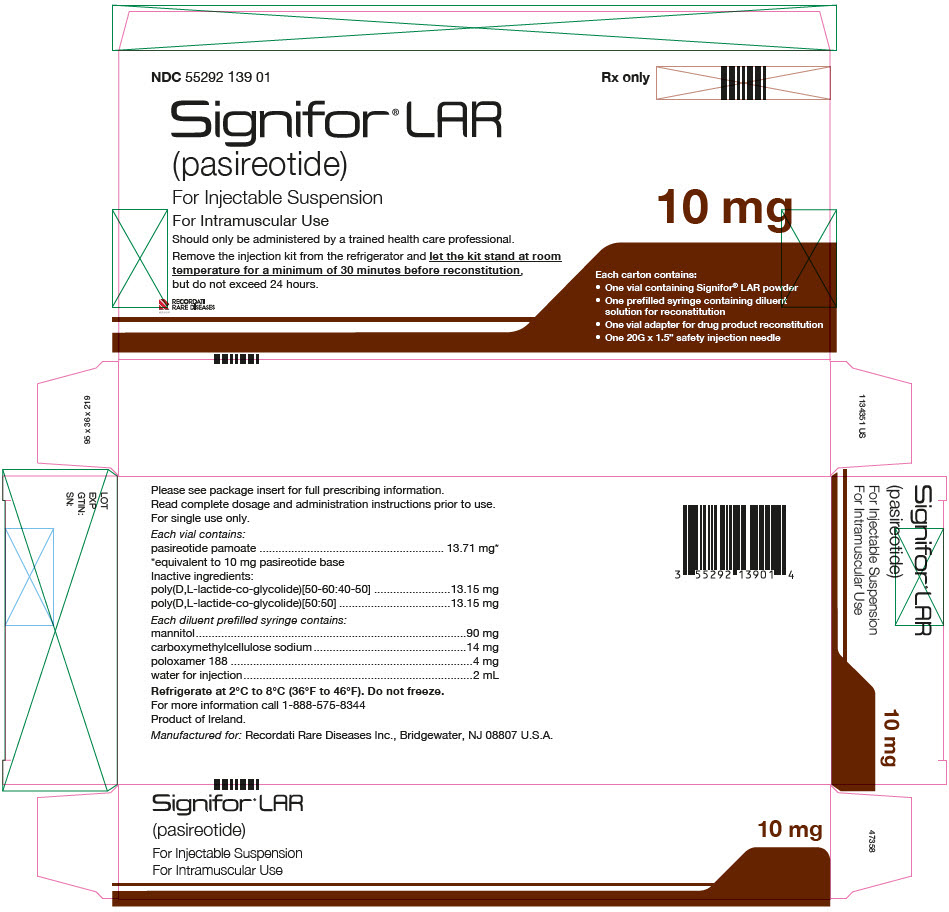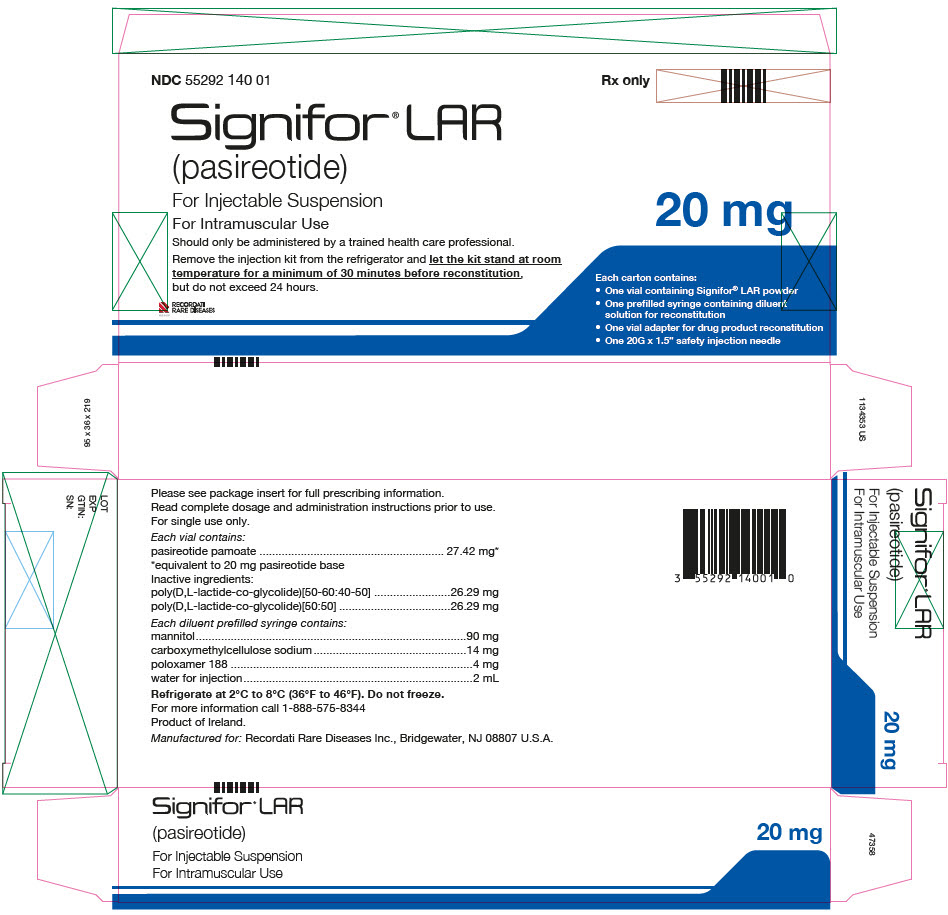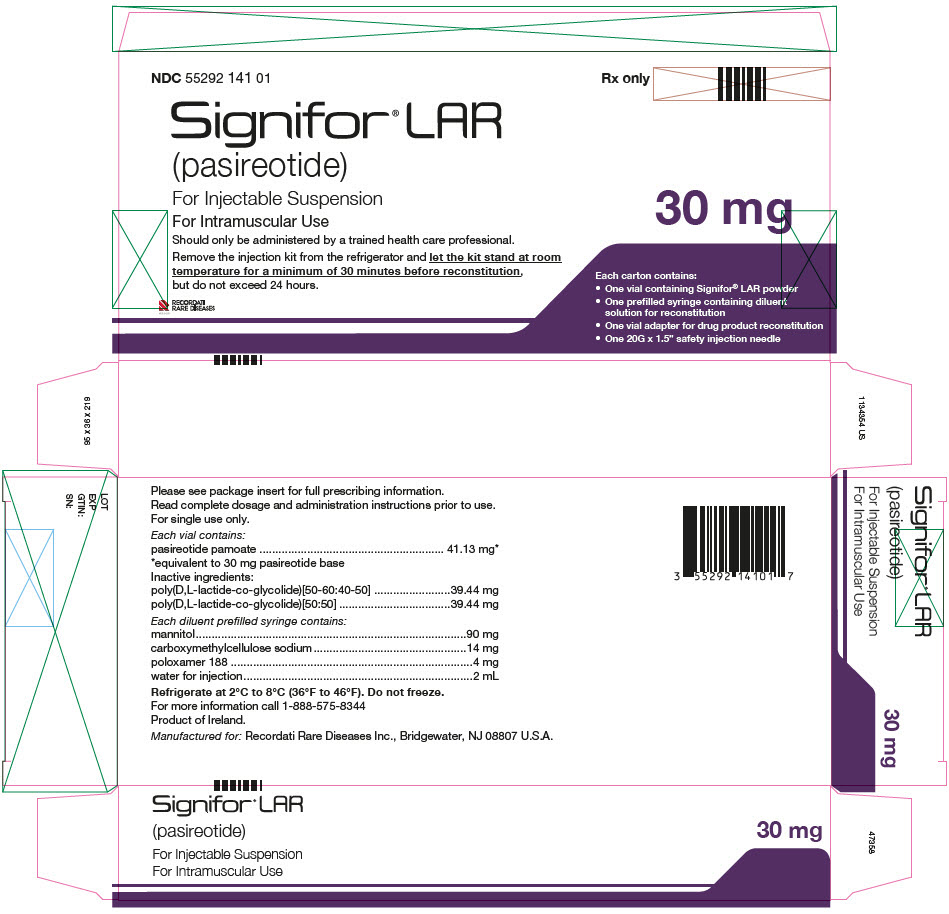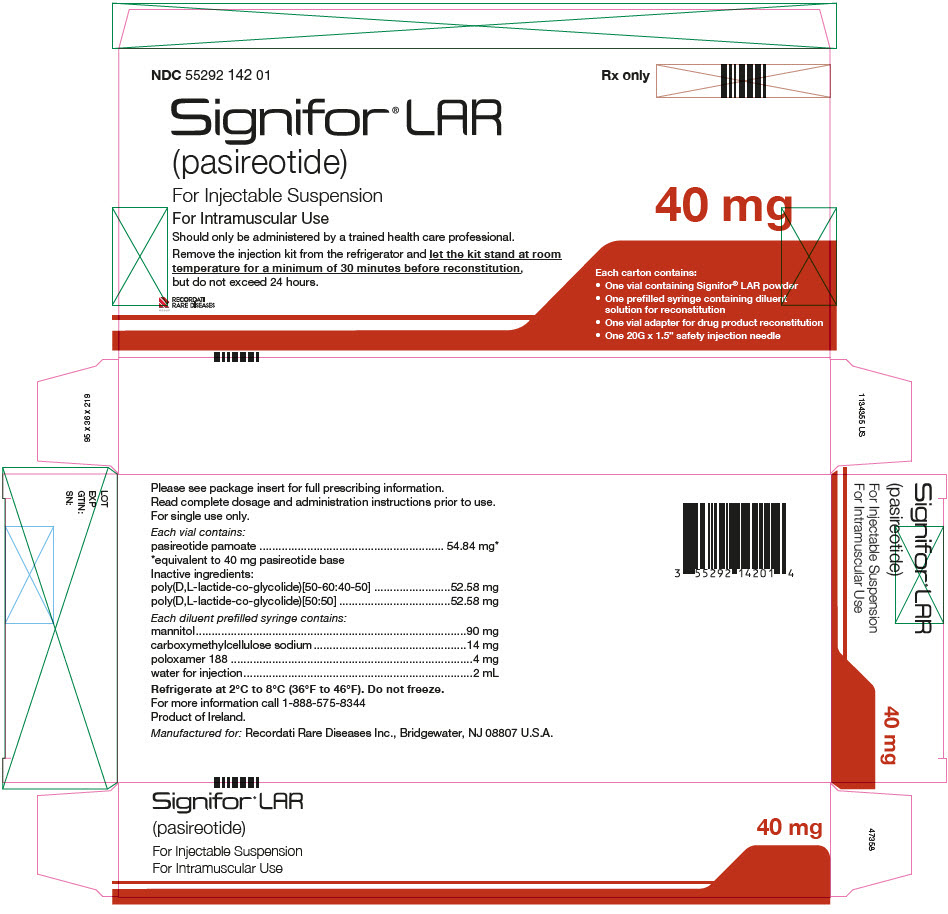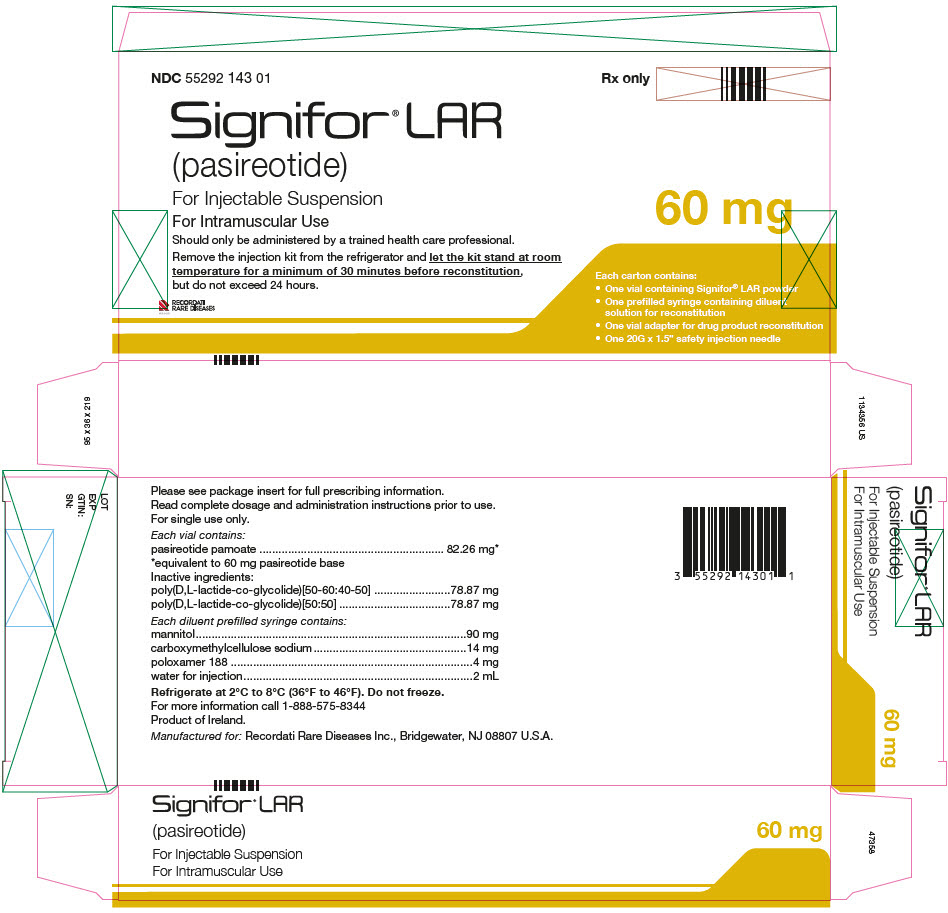 DRUG LABEL: Signifor LAR
NDC: 55292-139 | Form: KIT | Route: INTRAMUSCULAR
Manufacturer: Recordati Rare Diseases, Inc.
Category: prescription | Type: HUMAN PRESCRIPTION DRUG LABEL
Date: 20240716

ACTIVE INGREDIENTS: PASIREOTIDE 5 mg/1 mL
INACTIVE INGREDIENTS: DL-LACTIDE AND GLYCOLIDE (50:50) COPOLYMER 63000 ACID; DL-LACTIDE AND GLYCOLIDE (50:50) COPOLYMER 12000 ACID; MANNITOL 45 mg/1 mL; CARBOXYMETHYLCELLULOSE SODIUM, UNSPECIFIED 7 mg/1 mL; POLOXAMER 188 2 mg/1 mL; WATER 1 mL/1 mL

HIGHLIGHTS OF PRESCRIBING INFORMATION

These highlights do not include all the information needed to use SIGNIFOR LAR safely and effectively. See full prescribing information for SIGNIFOR LAR.
SIGNIFOR® LAR (pasireotide) for injectable suspension, for intramuscular use
Initial U.S. Approval: 2012

RECENT MAJOR CHANGES

Warnings and Precautions, Steatorrhea and Malabsorption of Dietary Fats (5.6) | 7/2024

1 INDICATIONS AND USAGE

SIGNIFOR LAR is a somatostatin analog indicated for the treatment of:

- Patients with acromegaly who have had an inadequate response to surgery and/or for whom surgery is not an option. (1.1)
- Patients with Cushing's disease for whom pituitary surgery is not an option or has not been curative. (1.2)

2 DOSAGE AND ADMINISTRATION

- Evaluate fasting plasma glucose (FPG), hemoglobin A1c (HbA1c), liver enzyme tests, electrocardiogram (ECG), serum magnesium, and serum potassium prior to starting. (2.1)
- Optimize glucose control in patients with poorly controlled diabetes mellitus prior to starting. (2.1)
- Must be administered by a health care professional only by intramuscular injection in the right or left gluteus immediately after reconstitution. (2.2)
- Initial Dose:
  - Acromegaly: The initial dose is 40 mg by intramuscular injection once every 4 weeks (every 28 days). (2.3)
  - Cushing's Disease: The initial dose is 10 mg by intramuscular injection once every 4 weeks (every 28 days). (2.3)
- Adjust dose based on response and tolerability. (2.4)
- Patients with Hepatic Impairment:
  - Child-Pugh B:
    - Acromegaly: Recommended initial dose is 20 mg once every 4 weeks and maximum dose is 40 mg once every 4 weeks (2.5, 8.6)
    - Cushing's Disease: Recommended initial dose is 10 mg once every 4 weeks and maximum dose is 20 mg once every 4 weeks (2.5, 8.6)
  - Child-Pugh C: Avoid use in these patients (2.5, 8.6)
- Follow reconstitution and administration instructions. (2.6)

3 DOSAGE FORMS AND STRENGTHS

SIGNIFOR LAR for injectable suspension: 10 mg, 20 mg, 30 mg, 40 mg, and 60 mg, powder in a vial to be reconstituted with the provided 2 mL diluent. (3)

4 CONTRAINDICATIONS

None. (4)

5 WARNINGS AND PRECAUTIONS

- Hyperglycemia, Diabetes, and Ketoacidosis: Sometimes severe. Monitor glucose levels as clinically appropriate during therapy. Monitor glucose levels more frequently in the months that follow initiation or discontinuation of SIGNIFOR LAR therapy and following SIGNIFOR LAR dose adjustment. Use anti-diabetic treatment if indicated.If ketoacidosis is suspected, discontinue SIGNIFOR LAR and promptly evaluate and treat the patient. (2.1, 5.1)
- Bradycardia and QT Prolongation: Use with caution in at-risk patients; evaluate ECG and electrolytes prior to dosing and periodically while on treatment. (2.1, 5.2, 7.1)
- Liver Test Elevations: Evaluate liver enzyme tests prior to and during treatment. (2.1, 5.3)
- Cholelithiasis and Complications of Cholelithiasis: Monitor periodically. Discontinue if complications of cholelithiasis are suspected. (5.4)
- Pituitary Hormone Deficiency(ies): Monitor for occurrence periodically and treat if clinically indicated. (5.5)
- Steatorrhea and Malabsorption of Dietary Fats: New onset steatorrhea, stool discoloration, loose stools, abdominal bloating, and weight loss may occur. If new occurrence or worsening of these symptoms are reported, evaluate for potential pancreatic exocrine insufficiency (5.6)

6 ADVERSE REACTIONS

Adverse drug reactions associated with SIGNIFOR LAR and occurring in ≥ 20% of patients were diarrhea, cholelithiasis, hyperglycemia, and diabetes mellitus. (6)

To report SUSPECTED ADVERSE REACTIONS, contact Recordati Rare Diseases Inc. at 1-888-575-8344 or FDA at 1-800-FDA-1088 or www.fda.gov/medwatch.

7 DRUG INTERACTIONS

- Drugs that Prolong QT: Use with caution in patients who are at significant risk of developing QTc prolongation. (5.2, 7.1)
- Cyclosporine: Consider additional monitoring. (7.2)
- Bromocriptine: Consider bromocriptine dose reduction. (7.2)

8 USE IN SPECIFIC POPULATIONS

- Females and Males of Reproductive Potential: Advise premenopausal females of the potential for an unintended pregnancy (8.3)

FULL PRESCRIBING INFORMATION

1 INDICATIONS AND USAGE

1.1 Acromegaly

SIGNIFOR LAR is indicated for the treatment of patients with acromegaly who have had an inadequate response to surgery and/or for whom surgery is not an option.

1.2 Cushing's Disease

SIGNIFOR LAR is indicated for the treatment of patients with Cushing's disease for whom pituitary surgery is not an option or has not been curative.

2 DOSAGE AND ADMINISTRATION

2.1 Recommended Baseline Evaluations Prior to Initiation of SIGNIFOR LAR

Prior to the initiation of SIGNIFOR LAR, it is recommended that patients have the following baseline evaluations:

- Fasting plasma glucose (FPG) and hemoglobin A1c (HbA1c) [see Warnings and Precautions (5.1)]
- Liver tests [see Warnings and Precautions (5.3)]
- Electrocardiogram (ECG), serum potassium and serum magnesium levels [see Warnings and Precautions (5.2)]

Patients with poorly controlled diabetes mellitus, who have inadequate glucose control, should have anti-diabetic therapy optimized prior to starting SIGNIFOR LAR [see Warnings and Precautions (5.1)].

2.2 Important Administration Instructions

SIGNIFOR LAR must be reconstituted by a trained healthcare professional immediately before use. Illustrations on reconstitution are found in Instructions for Use [see Dosage and Administration (2.6)].

SIGNIFOR LAR must be inspected visually before use. The suspension should appear free of foreign particulates and should be homogeneous after mixing.

SIGNIFOR LAR must be administered by a trained healthcare professional only by intramuscular injection in the right or left gluteus immediately after reconstitution. SIGNIFOR LAR must never be administered intravenously.

2.3 Recommended Initial Dose

Acromegaly

The recommended initial dose of SIGNIFOR LAR for the treatment of acromegaly is 40 mg administered by intramuscular injection once every 4 weeks (every 28 days) [see Dosage and Administration (2.6)].

Cushing's Disease

The recommended initial dose of SIGNIFOR LAR for the treatment of Cushing's disease is 10 mg administered by intramuscular injection once every 4 weeks (every 28 days) [see Dosage and Administration (2.6)].

2.4 Dose Adjustment and Monitoring

Acromegaly

The dose may be increased to a maximum of 60 mg for patients who have not normalized growth hormone (GH) and/or age and sex adjusted insulin-like growth factor-1 (IGF-1) levels after 3 months of treatment with SIGNIFOR LAR at 40 mg and who tolerate this dose.

Management of SIGNIFOR LAR-related adverse reactions or over-response to treatment (age and sex adjusted IGF-1 less than the lower limit of normal) may require dose reduction. The dose may be decreased, either temporarily or permanently, by 20 mg decrements [see Warnings and Precautions (5)].

Cushing's Disease

Following 4 months of treatment with the initial dose of 10 mg once every 28 days, the dose may be increased for patients who have not normalized 24-hour urinary free cortisol (UFC) and who tolerate this dose, up to a maximum dose of 40 mg once every 28 days.

Management of suspected adverse reactions or over-response to treatment (e.g., cortisol levels less than the lower limit of the normal range or in the low part of the normal range in patients with symptoms suggestive of adrenal insufficiency) may require dose reduction to the previous tolerated dose, dose interruption, or drug discontinuation of SIGNIFOR LAR. For patients treated with 10 mg once every 28 days, the dose may be either interrupted or discontinued [see Warnings and Precautions (5)].

2.5 Dose in Patients With Hepatic Impairment

For patients with moderately impaired hepatic function (Child-Pugh B) [see Use in Specific Populations (8.6)]:

- Acromegaly: The recommended initial dose for acromegaly patients with moderately impaired hepatic function is 20 mg once every 4 weeks and the maximum recommended dose is 40 mg once every 4 weeks.
- Cushing's Disease: The recommended initial dose for Cushing's disease patients with moderately impaired hepatic function is 10 mg once every 4 weeks and the maximum recommended dose is 20 mg once every 4 weeks.

Avoid use in patients with severe hepatic impairment (Child-Pugh C) [see Use in Specific Populations (8.6)].

2.6 Reconstitution and Intramuscular Injection Instructions

After reconstitution of the SIGNIFOR LAR vial with the provided 2 mL diluent, the intramuscular injectable suspension will have a final concentration of:

Strength per Vial | Final Concentration When Reconstituted (total product strength per total volume) | Final Concentration When Reconstituted (per mL)
10 mg | 10 mg/2 mL | 5 mg/mL
20 mg | 20 mg/2 mL | 10 mg/mL
30 mg | 30 mg/2 mL | 15 mg/mL
40 mg | 40 mg/2 mL | 20 mg/mL
60 mg | 60 mg/2 mL | 30 mg/mL

The entire contents of the reconstituted solution should be administered immediately.

PAY PARTICULAR ATTENTION:

There are 2 critical steps in the reconstitution of SIGNIFOR LAR. Not following these 2 steps could result in failure to deliver the drug appropriately.

1) The injection kit must reach room temperature (see Step 1 in Instructions for Use). Remove the SIGNIFOR LAR injection kit from refrigerated storage and let the kit stand at room temperature for a minimum of 30 minutes before reconstitution, but do not exceed 24 hours.

2) After adding the diluent solution, shake the vial moderately in a horizontal direction for a minimum of 30 seconds until uniform suspension is formed (see Step 4 in Instructions for Use).

The following items are included in the injection kit:

a) One vial containing SIGNIFOR LAR powder

b) One prefilled syringe containing the diluent solution for reconstitution

c) One vial adapter for drug product reconstitution

d) One safety injection needle (20G x 1.5")

Figure 1. Items Included in Injection Kit

SIGNIFOR LAR suspension must only be reconstituted immediately before administration.

Follow the directions in the Instructions for Use to ensure proper reconstitution of SIGNIFOR LAR before intramuscular injection.

SIGNIFOR LAR should only be administered by a trained healthcare professional.

Instructions for Use

Step 1
Remove the SIGNIFOR LAR for injectable suspension kit from refrigerated storage.
PAY PARTICULAR ATTENTION: It is essential to start the reconstitution process only after the injection kit has reached room temperature. Let the kit stand at room temperature for at least 30 minutes before starting reconstitution, but not more than 24 hours.
Note: The kit can be re-refrigerated if needed.

Step 2
Remove the plastic cap from the vial and clean the rubber stopper with an alcohol wipe.

Remove the lid film of the vial adapter packaging, but do NOT remove the vial adapter from its packaging.
Holding the vial adapter packaging, position the vial adapter on top of the vial and push it fully down so that it snaps in place. You will hear an audible "click" when the vial adapter snaps in place.

Lift the packaging off the vial adapter with a vertical movement.

Step 3
Remove the cap from the syringe prefilled with diluent solution and screw the syringe onto the vial adapter.

Slowly push the plunger all the way down to transfer all the diluent solution in the vial.

Step 4
ATTENTION: Keep the plunger pressed and shake the vial moderately in a horizontal direction for a minimum of 30 seconds so that the powder is completely suspended. Repeat moderate shaking for another 30 seconds if the powder is not completely suspended.

Step 5
Turn the syringe and vial upside down, slowly pull the plunger back and draw the entire content from the vial into the syringe.

Unscrew the syringe from the vial adapter.

Step 6
Screw the safety injection needle onto the syringe.

Pull the protective cover straight off the needle.
To avoid sedimentation and maintain a uniform suspension, you may gently shake the syringe.
Gently tap the syringe to remove any visible bubbles and expel them from the syringe.
The reconstituted SIGNIFOR LAR is now ready for immediate administration.

Step 7
SIGNIFOR LAR must only be given by intramuscular injection and NEVER intravenously.
Prepare the injection site by wiping with an alcohol wipe.
Insert the needle fully into the left or right gluteus at a 90° angle to the skin.
Slowly pull back the plunger to check that no blood vessel has been penetrated (reposition if a blood vessel has been penetrated).
Slowly depress the plunger until the syringe is empty. Withdraw the needle from the injection site and activate the safety guard (as shown in Step 8).

Step 8
Activate the safety guard over the needle using 1 of the 2 methods shown:
• either press the hinged section of the safety guard down onto a hard surface (Figure A),
• or push the hinge forward with your finger (Figure B).
An audible "click" will confirm proper activation of the safety guard.
Dispose of syringe immediately in a sharps container.
Any unused product or waste material should be disposed of in accordance with local requirements.

2.7 Missed Dose

If a dose is missed and the patient returns prior to the next scheduled dose, a dose may be given up to but no later than 14 days prior to the next dose.

3 DOSAGE FORMS AND STRENGTHS

SIGNIFOR LAR for injectable suspension: 10 mg, 20 mg, 30 mg, 40 mg, or 60 mg of slightly yellow to yellow powder in a vial and 2 mL diluent.

4 CONTRAINDICATIONS

None.

5 WARNINGS AND PRECAUTIONS

5.1 Hyperglycemia, Diabetes, and Ketoacidosis

SIGNIFOR LAR can cause increases in blood glucose levels which are sometimes severe. There have been postmarketing cases of ketoacidosis with SIGNIFOR LAR in patients with history of diabetes and in patients without history of diabetes.

In the acromegalic patient study, 5 patients naïve to drug therapy treated with SIGNIFOR LAR (2 of whom were normoglycemic at baseline) and none in the active comparator group were hospitalized for hyperglycemia (blood glucose range 359-506 mg/dL). Two additional patients who had received active comparator in the main trial and were switched to SIGNIFOR LAR in the extension trial, were hospitalized for elevated glucose levels while on SIGNIFOR LAR; one of those patients developed diabetic ketoacidosis. In the Cushing's disease study, 2 patients were hospitalized for elevated blood glucose.

In clinical studies for acromegaly and Cushing's disease, SIGNIFOR LAR caused an increase in the incidence of diabetes and prediabetes. A majority of patients, including those with normal glucose tolerance, prediabetes and diabetes, experienced increased glucose levels within the first 3 months of treatment [see Adverse Reactions (6.1)]. In the drug-naïve acromegaly study, the prevalence of diabetes increased from 30% at baseline to 60% at Month 12. In the study evaluating acromegaly patients previously treated with somatostatin analogs, the prevalence of diabetes increased from 71% at baseline to 87% at Month 6 in patients treated with SIGNIFOR LAR 40 mg, and from 60% to 84% in patients treated with SIGNIFOR LAR 60 mg. In the Cushing's disease study, the prevalence of diabetes increased from 40% at baseline to 56% at Month 12.

Patients with poor baseline glycemic control are at higher risk of developing severe hyperglycemia. Assess FPG and HbA1c prior to starting treatment with SIGNIFOR LAR [see Dosage and Administration (2.1)]. In patients with poorly controlled diabetes mellitus, optimize anti-diabetic treatment before SIGNIFOR LAR initiation. Monitor blood glucose weekly for the first 3 months after initiating SIGNIFOR LAR and the first 4- to 6 weeks after dose increases. Continue monitoring thereafter, as clinically appropriate.

Patients who develop significant hyperglycemia on SIGNIFOR LAR may require initiation of anti-diabetic treatment or adjustment in their current anti-diabetic treatment. The optimal treatment for the management of SIGNIFOR LAR-induced hyperglycemia is not known. If hyperglycemia cannot be controlled despite medical management, reduce the dose of SIGNIFOR LAR or discontinue SIGNIFOR LAR. Assess FPG and HbA1c after SIGNIFOR LAR discontinuation, if indicated. Patients receiving anti-diabetic treatment may require more frequent blood glucose monitoring and dose adjustment to their anti-diabetic drug therapy to mitigate the risk of hypoglycemia after discontinuing SIGNIFOR LAR.

Patients who present with signs and symptoms consistent with severe metabolic acidosis should be assessed for ketoacidosis regardless of diabetes history. In some reported post-marketing cases of ketoacidosis in patients taking SIGNIFOR LAR, factors predisposing to ketoacidosis such as acute illness, infection, pancreatic disorders (e.g., pancreatic malignancy or pancreatic surgery), and alcohol abuse were present. If ketoacidosis is suspected, discontinue SIGNIFOR LAR and promptly evaluate and treat the patient.

5.2 Bradycardia and QT Prolongation

Bradycardia

Bradycardia has been reported with the use of SIGNIFOR LAR [see Adverse Reactions (6.1)]. Patients with cardiac disease and/or risk factors for bradycardia, such as history of clinically significant bradycardia, high-grade heart block, or concomitant use of drugs associated with bradycardia, should be monitored. Adjustments in the dose of drugs known to slow the heart rate (e.g., beta-blockers, calcium channel blockers) and correction of electrolyte disturbances may be necessary when initiating or during the course of SIGNIFOR LAR treatment.

QT Prolongation

In cardiac electrophysiology studies (i.e., thorough QT studies) with pasireotide via subcutaneous route, QT prolongation occurred at therapeutic and supra-therapeutic doses [see Clinical Pharmacology (12.2)].

In the clinical studies, a corrected QT interval (i.e., QTcF) of greater than 480 ms was reported in 6 patients and an increase in the QTcF from baseline of greater than 60 ms was reported for seven patients on SIGNIFOR LAR. No patient on SIGNIFOR LAR had a QTcF value of greater than 500 ms [see Adverse Reactions (6.1), Clinical Pharmacology (12.2)].

SIGNIFOR LAR should be used with caution in patients who are at significant risk of developing prolongation of the QT interval, such as those listed below:

- with congenital long QT prolongation
- with uncontrolled or significant cardiac disease including recent myocardial infarction, congestive heart failure, unstable angina or clinically significant bradycardia
- on anti-arrhythmic therapy or other substances that are known to lead to QT prolongation
- with hypokalemia and/or hypomagnesemia

A baseline ECG is recommended prior to initiating therapy with SIGNIFOR LAR. Monitoring for an effect on the QT interval at the time of maximum drug concentration (21 days after injection) should be obtained in patients at risk. Hypokalemia or hypomagnesemia must be corrected prior to initiating SIGNIFOR LAR and should be monitored periodically during therapy.

5.3 Liver Test Elevations

Increases in liver enzymes have been observed with SIGNIFOR LAR. In all Phase 3 acromegaly studies and across all doses, alanine aminostransferase (ALT) or aspartate aminotransferase (AST) elevations greater than 3 times the upper limit of normal (ULN) were observed in 4% of acromegaly patients and ALT or AST elevations greater than 5 times the ULN were observed in 1% of acromegaly patients treated with SIGNIFOR LAR.

In the Phase 3 Cushing's disease study and across all doses, ALT or AST elevations greater than 3 times the ULN were observed in 14% of Cushing's disease patients and ALT or AST elevations greater than 5 times the ULN were observed in 5% of Cushing's disease patients treated with SIGNIFOR LAR.

Assessment of liver function is recommended prior to treatment with SIGNIFOR LAR , and after the first 2- to 3 weeks, then monthly for 3 months. Thereafter, liver function should be monitored as clinically indicated. Patients who develop increased transaminase levels, should be monitored until values return to pre-treatment levels. Treatment with SIGNIFOR LAR should be discontinued if signs or symptoms suggestive of clinically significant liver impairment develop. Following discontinuation of treatment with SIGNIFOR LAR, patients should be monitored until resolution. Treatment should not be restarted, if the liver function abnormalities are suspected to be related to SIGNIFOR LAR.

5.4 Cholelithiasis and Complications of Cholelithiasis

Cholelithiasis was reported in 33% of drug-naïve and 10% of inadequately controlled (40 mg dose) acromegaly patients treated with SIGNIFOR LAR in clinical trials [see Adverse Reactions (6)]. Cholelithiasis was reported in 33% of Cushing's disease patients treated with SIGNIFOR LAR. There have been postmarketing reports of cholelithiasis (gallstones) resulting in complications, including cholecystitis or cholangitis and requiring cholecystectomy in patients taking SIGNIFOR LAR. Patients should be monitored periodically. If complications of cholelithiasis are suspected, discontinue SIGNIFOR LAR and treat appropriately.

5.5 Pituitary Hormone Deficiency(ies)

Suppression of anterior pituitary hormones may occur on SIGNIFOR LAR. Monitoring pituitary function (e.g., thyroid, adrenal, gonadal) prior to initiation of therapy with SIGNIFOR LAR, as well as periodically during treatment, as clinically appropriate, is recommended. Patients should be monitored for and instructed on the signs and symptoms of adrenal insufficiency during therapy. If adrenal insufficiency is suspected, it should be confirmed and treated per standard of care with exogenous glucocorticoids at replacement doses.

5.6 Steatorrhea and Malabsorption of Dietary Fats

New onset steatorrhea, stool discoloration and loose stools have been reported in patients receiving somatostatin analogs, including pasireotide products. Somatostatin analogs reversibly inhibit secretion of pancreatic enzymes and bile acids, which may result in malabsorption of dietary fats and subsequent symptoms of steatorrhea, loose stools, abdominal bloating, and weight loss. If new occurrence or worsening of these symptoms are reported in patients receiving SIGNIFOR LAR, evaluate patients for potential pancreatic exocrine insufficiency and manage accordingly.

6 ADVERSE REACTIONS

Clinically significant adverse reactions that appear in other sections of the labeling include:

- Hyperglycemia, Diabetes, and Ketoacidosis [see Warnings and Precautions (5.1)]
- Bradycardia and QT Prolongation [see Warnings and Precautions (5.2)]
- Liver Test Elevations [see Warnings and Precautions (5.3)]
- Cholelithiasis and Complications of Cholelithiasis [see Warnings and Precautions (5.4)]
- Pituitary Hormone Deficiency(ies) [see Warnings and Precautions (5.5)]
- Steatorrhea and Malabsorption of Dietary Fats [see Warnings and Precautions (5.6)]

6.1 Clinical Trials Experience

Because clinical trials are conducted under widely varying conditions, adverse reaction rates observed in clinical trials of a drug cannot be directly compared to rates in clinical trials of another drug and may not reflect the rates observed in practice.

Drug-Naïve Patients With Acromegaly

The data described in Table 1 are derived from an active-controlled trial in patients with acromegaly naïve to previous drug therapy [see Clinical Studies (14.1)]. The data reflect exposure of 178 patients with acromegaly to SIGNIFOR LAR for a mean duration of 43 weeks. In the overall study population, 52% were female and the average age of patients was 45 years.

Table 1 presents common adverse reactions associated with SIGNIFOR LAR in this study. These adverse reactions were not present at baseline or, if present, worsened from baseline and occurred in at least 5% of patients treated with SIGNIFOR LAR.

Table 1 – Adverse Reactions Occurring in Greater Than or Equal to 5% of Patients Exposed to SIGNIFOR LAR in Patients With Acromegaly Naïve to Drug Therapy
Adverse Reaction Type | SIGNIFOR LAR (40-60 mg) % N = 178 | Active Comparator % N = 180
Hyperglycemia Related Adverse Reactions
Hyperglycemia | 29 | 8
Diabetes mellitusa | 26 | 4
Blood glucose increased | 8 | 2
Glycosylated hemoglobin increased | 6 | 2
Hypoglycemia | 5 | 7
Gastrointestinal Related Adverse Reactions
Diarrhea | 39 | 45
Abdominal pain | 18 | 22
Nausea | 14 | 22
Abdominal distension | 12 | 12
Vomiting | 8 | 7
Abdominal pain upper | 6 | 8
Hepatobiliary Related Adverse Reactions
Cholelithiasis | 26 | 36
Cardiac Related Adverse Reactions
Sinus bradycardiab | 10 | 7
Hypertension | 8 | 7
Nervous System Related Adverse Reactions
Headache | 19 | 26
Dizziness | 10 | 11
Skin Related Adverse Reactions
Alopecia | 18 | 19
Infections Related Adverse Reactions
Nasopharyngitis | 16 | 16
Influenza | 8 | 4
Upper respiratory tract infection | 7 | 3
Cough | 5 | 8
Laboratory Related Adverse Reactions
Blood creatine phosphokinase increased | 13 | 12
Alanine aminotransferase increased | 8 | 4
Aspartate aminotransferase increased | 6 | 4
Lipase increased | 6 | 7
Weight decreased | 5 | 4
General and Injection-Site Related Adverse Reactions
Fatigue | 10 | 10
Injection-site reactionc | 7 | 7
Musculoskeletal and Connective Tissue Related Adverse Reactions
Arthralgia | 10 | 12
Back pain | 8 | 11
Pain in extremity | 7 | 4
Blood Related Adverse Reactions
Anemia | 6 | 6
aDiabetes mellitus includes the following PTs: diabetes mellitus and type 2 diabetes mellitus.
bSinus bradycardia includes the following PTs: bradycardia and sinus bradycardia.
cInjection-site reaction related AEs includes the following PTs: injection-site pain, injection-site reaction, injection-site haematoma, injection-site pruritus, injection-site swelling, injection-site erythema.

Other notable adverse reactions which occurred with a frequency of 5% or less for SIGNIFOR LAR were: adrenal insufficiency (3%); glucose tolerance impaired (1%); QT-prolongation (4%); blood amylase increased (2%).

Patients With Acromegaly Inadequately Controlled on Other Somatostatin Analogs at Baseline

The data described in Table 2 are derived from an active-controlled study in patients with acromegaly inadequately controlled at baseline on other somatostatin analogs [see Clinical Studies (14.2)]. These data reflect exposure of 63 and 62 patients to SIGNIFOR LAR 40 mg and 60 mg, respectively, for a mean duration of 24 weeks. In the overall study population, 56% were female and the average age of patients was 45 years.

Table 2 presents common adverse reactions associated with SIGNIFOR LAR in this study. These common adverse reactions were not present at baseline, or if present, worsened from baseline and occurred in at least 5% of patients treated with SIGNIFOR LAR.

Table 2 – Adverse Reactions Occurring in Greater Than or Equal to 5% of Patients Exposed to SIGNIFOR LAR in Patients With Acromegaly Previously Treated With Other Somatostatin Analogs
Adverse Drug Reactions | SIGNIFOR LAR 40 mg % N = 63 | SIGNIFOR LAR 60 mg % N = 62 | Active Comparators % N = 66
Hyperglycemia Related Adverse Reactions
Hyperglycemia | 33 | 30 | 14
Diabetes mellitusa | 21 | 31 | 9
Blood glucose increased | 5 | 7 | 0
Hypoglycemia | 3 | 7 | 0
Gastrointestinal Related Adverse Reactions
Diarrhea | 16 | 19 | 5
Abdominal pain | 8 | 8 | 3
Nausea | 3 | 7 | 3
Hepatobiliary Related Adverse Reactions
Cholelithiasis | 10 | 13 | 14
Cardiac Related Adverse Reactions
Atrioventricular block first degree | 6 | 0 | 0
Nervous System Related Adverse Reactions
Headache | 14 | 3 | 5
Dizziness | 8 | 2 | 3
Skin and Subcutaneous Tissue Related Adverse Reactions
Alopecia | 2 | 7 | 0
Infections Related Adverse Reactions
Nasopharyngitis | 6 | 11 | 3
Blood Related Adverse Reactions
Anemia | 6 | 3 | 3
aDiabetes mellitus includes the following PTs: diabetes mellitus and type 2 diabetes mellitus.

Other notable adverse reactions which occurred with a frequency of 5% or less in the SIGNIFOR LAR 40 mg, SIGNIFOR LAR 60 mg arm, respectively, were adrenal insufficiency (2% and 0%) and glucose tolerance impaired (3% and 5%).

Patients With Cushing's Disease

The data described in Table 3 are derived from a randomized clinical study in 150 patients with Cushing's disease [see Clinical Studies (14.3)]. These data reflect exposure of 74 and 76 patients to SIGNIFOR LAR at a starting dose of 10 mg and 30 mg once every 28 days, respectively, for a mean duration of 68 weeks. In the overall study population, 79% of patients were female and the average age was 39 years at study entry.

Table 3 presents common adverse reactions which were not present at baseline or, if present, worsened from baseline and occurred in at least 5% of patients treated with SIGNIFOR LAR.

Table 3 – Adverse Reactions Occurring in Greater Than or Equal to 5% of Patients Exposed to SIGNIFOR LAR in Patients With Cushing's Disease
Adverse Reactions | Overall % N = 150
Endocrine Related Adverse Reactions
Adrenal insufficiency | 7
Blood cortisol decreased | 5
Hyperglycemia Related Adverse Reactions
Hyperglycemia | 47
Diabetes mellitusa | 27
Hypoglycemia | 15
Blood glucose increased | 9
Glycosylated hemoglobin (HbA1C) increased | 5
Gastrointestinal Related Adverse Reactions
Diarrhea | 39
Nausea | 21
Abdominal painb | 23
Constipation | 7
Abdominal distension | 5
Flatulence | 5
Vomiting | 5
Hepatobiliary Related Adverse Reactions
Cholelithiasis | 33
Gamma-glutamyltransferase increased | 9
Alanine aminotransferase increased | 7
Cardiac Related Adverse Reactions
Hypertension | 15
Hypotension | 6
Sinus bradycardiac | 5
General Related Adverse Reactions
Fatigued | 27
Edema peripheral | 14
Musculoskeletal and Connective Tissue Related Adverse Reactions
Back pain | 11
Arthralgia | 8
Pain in extremity | 7
Myalgia | 5
Metabolism and Nutrition Related Adverse Reactions
Decreased appetite | 10
Hyperuricemia | 7
Hypercholesterolemia | 6
Blood Related Adverse Reactions
Anemia | 5
aDiabetes mellitus consists of the two terms: diabetes mellitus and type 2 diabetes mellitus.
bAbdominal pain includes the term abdominal pain upper.
cSinus bradycardia includes the term bradycardia.
dFatigue includes the term asthenia.

Other adverse reactions which occurred at a frequency less than 5% were cholestasis (4%), glucose tolerance impaired (3%), aspartate aminotransferase increased (3%), vomiting (3%), lipase increased (3%), injection-site reactions (2%), ECG QT prolonged (1%), cholecystitis (1%), amylase increased (1%), and prothrombin time prolonged (1%).

Hyperglycemia

The average FPG levels in patients with acromegaly naïve to drug therapy study [see Clinical Studies (14.1)] across visits is shown in Figure 2 below.

Figure 2. Mean Fasting Plasma Glucose (mg/dL) By Visit in the Study of Patients With Acromegaly Naïve to Drug Therapy [Numbers of patients with a glucose value at the given timepoint in the SIGNIFOR LAR/Active comparator arms are displayed as xxx/xxx on the x axis.]

Pancreatic Enzyme Elevation and Pancreatitis

Asymptomatic elevations in lipase and alpha amylase were observed in 30% and 20% of patients receiving SIGNIFOR LAR in the drug naïve study in acromegaly, and in 1% and 3% of patients receiving SIGNIFOR LAR in the study of acromegaly patients previously treated. In the drug-naïve study, 2 acromegaly patients receiving SIGNIFOR LAR developed pancreatitis. In the Cushing's disease study, increased lipase was observed in 4% of patients, and 1 patient developed pancreatitis. Pancreatitis is a potential adverse reaction associated with the use of SIGNIFOR LAR due to the association between cholelithiasis and acute pancreatitis.

6.2 Postmarketing Experience

Additional adverse reactions have been identified during post-approval use of SIGNIFOR LAR. Because these reactions are reported voluntarily from a population of uncertain size, it is generally not possible to reliably estimate their frequency or establish a causal relationship to drug exposure.

- Cholelithiasis resulting in complications, including cholecystitis and cholangitis, which have sometimes required cholecystectomy

7 DRUG INTERACTIONS

7.1 Effect of Other Drugs on SIGNIFOR LAR

Drugs That Prolong QT

Co-administration of drugs that prolong the QT interval with SIGNIFOR LAR may have additive effects on the prolongation of the QT interval. Monitoring effects on the QT interval at 21 days is recommended [see Warnings and Precautions (5.2)].

7.2 Effect of SIGNIFOR LAR on Other Drugs

Cyclosporine

Concomitant administration of cyclosporine with SIGNIFOR LAR may decrease the relative bioavailability of cyclosporine and, therefore, dose adjustment of cyclosporine to maintain therapeutic levels may be necessary.

Bromocriptine

Co-administration of SIGNIFOR LAR with bromocriptine may increase the blood levels of bromocriptine. Dose reduction of bromocriptine may be necessary.

8 USE IN SPECIFIC POPULATIONS

8.1 Pregnancy

Risk Summary

The limited data with SIGNIFOR LAR in pregnant women are insufficient to inform a drug-associated risk for major birth defects and miscarriage. In embryo-fetal development studies in rabbits, findings indicating a developmental delay were observed with subcutaneous administration of pasireotide during organogenesis at doses less than the exposure in humans at the highest recommended dose; maternal toxicity was not observed at this dose (see Data).

The estimated background risk of major birth defects and miscarriage for the indicated population is unknown. In the U.S. general population, the estimated background risk of major birth defects and miscarriage in clinically recognized pregnancies is 2%-4% and 15%-20%, respectively.

Data

Animal Data

In embryo-fetal development studies in rats given 1 mg/kg/day, 5 mg/kg/day, and 10 mg/kg/day subcutaneously throughout organogenesis, maternal toxicity was observed at all doses, including the lowest dose tested which had exposures 12 times higher than that at the maximum therapeutic dose based on area under the curve (AUC) comparisons across species. An increased incidence of early/total resorptions and malrotated limbs was observed in rats at 10 mg/kg/day. At 10 mg/kg/day in rats, the maternal systemic exposure (AUC) was 42179 ng*hr/mL, approximately 106 times the exposure in humans at the highest recommended dose of 60 mg SIGNIFOR LAR administered as an intramuscular injection once every 4 weeks.

In embryo-fetal development studies in rabbits given 0.05 mg/kg/day, 1 mg/kg/day, and 5 mg/kg/day subcutaneously through organogenesis, maternal toxicity was observed at 1 mg/kg/day, at a maternal systemic exposure (AUC) of 1906 ng*hr/mL, approximately 5 times higher than the maximum human therapeutic exposure. An increased incidence of unossified forepaw phalanx, indicative of a developmental retardation, was observed in rabbits at 0.05 mg/kg/day, with maternal systemic exposures less than the systemic exposure in humans at the highest recommended dose.

In pre- and post-natal developmental studies in rats given subcutaneous doses of 2 mg/kg/day, 5 mg/kg/day, and 10 mg/kg/day during gestation through lactation and weaning, maternal toxicity was observed at all doses including the lowest dose (9 times higher than the maximum therapeutic dose based on surface area comparisons across species). Retardation of physiological growth, attributed to GH inhibition was observed at 2 mg/kg/day during a pre- and post-natal study in rats. After weaning, body weight gains in the rat pups (F1 generation) exposed to pasireotide were comparable to controls, showing reversibility of this developmental delay.

8.2 Lactation

Risk Summary

There is no information available on the presence of SIGNIFOR LAR in human milk, the effects of the drug on the breastfed infant, or the effects of the drug on milk production. Studies show that pasireotide administered subcutaneously passes into the milk of lactating rats; however, due to species-specific differences in lactation physiology, animal data may not reliably predict drug levels in human milk (see Data). The developmental and health benefits of breastfeeding should be considered along with the mother's clinical need for SIGNIFOR LAR, and any potential adverse effects on the breastfed child from SIGNIFOR LAR or from the underlying maternal condition.

Data

Available data in animals have shown excretion of pasireotide in milk. After a single 1 mg/kg [^14C]-pasireotide subcutaneous dose to lactating rats, the transfer of radioactivity into milk was observed. The overall milk:plasma (M/P) exposure ratio of total radioactivity was 0.28, based on AUC0-∞ values.

8.3 Females and Males of Reproductive Potential

Discuss the potential for unintended pregnancy with premenopausal women as the therapeutic benefits of a reduction in GH levels and normalization of IGF-1 in acromegalic females treated with pasireotide may lead to improved fertility.

Similarly, the therapeutic benefits of a reduction or normalization of serum cortisol levels in female patients with Cushing's disease treated with pasireotide may also lead to improved fertility.

8.4 Pediatric Use

Safety and effectiveness of SIGNIFOR LAR have not been established in pediatric patients.

8.5 Geriatric Use

Clinical studies of SIGNIFOR LAR did not include sufficient numbers of subjects aged 65 and over to determine whether they respond differently from younger subjects. Other reported clinical experience has not identified differences in responses between the elderly and younger patients. In general, dose selection for an elderly patient should be cautious, usually starting at the low end of the dosing range, reflecting the greater frequency of decreased hepatic, renal, or cardiac function, and of concomitant disease or other drug therapy.

8.6 Hepatic Impairment

Dose adjustment is not required in patients with mild impaired hepatic function (Child-Pugh A), but is required for patients with moderately impaired hepatic function (Child-Pugh B). The safety and efficacy of SIGNIFOR LAR have not been established in patients with severe hepatic impairment (Child-Pugh C). No dosage recommendation can be given for patients with severe hepatic impairment (Child-Pugh C) [see Dosage and Administration (2.5), Clinical Pharmacology (12.3)].

8.7 Renal Impairment

Clinical studies of SIGNIFOR LAR in patients with renal impairment have not been conducted. On the basis of studies with pasireotide given subcutaneously, dosage adjustment is not needed in patients with renal impairment [see Clinical Pharmacology (12.3)].

10 OVERDOSAGE

In the event of overdosage, it is recommended that appropriate supportive treatment be initiated, as dictated by the patient's clinical status, until resolution of the symptoms.

Up-to-date information about the treatment of overdose can be obtained from a certified Regional Poison Center. In the event of an overdose, contact the National Capital Poison Center at 1-800-222-1222 or www.poison.org.

11 DESCRIPTION

SIGNIFOR LAR (pasireotide) for injectable suspension is a long-acting release form of pasireotide pamoate, as powder to be suspended in the provided diluent immediately prior to intramuscular injection. SIGNIFOR LAR contains pasireotide, a somatostatin analog in the form of pasireotide pamoate (pamoic acid salt). Pasireotide is a cyclohexapeptide with pharmacologic properties mimicking those of the natural hormone somatostatin. Pasireotide pamoate has a chemical name of (2-Aminoethyl) carbamic acid (2R,5S,8S,11S,14R,17S,19aS)-11-(4-aminobutyl)-5-benzyl-8-(4-benzyloxybenzyl)-14-(1H-indol-3-ylmethyl)-4,7,10,13,16,19-hexaoxo-17-phenyloctadecahydro-3a,6,9,12,15,18-hexaazacyclopentacyclooctadecen-2-yl ester pamoic acid salt.

The molecular formula of pasireotide pamoate is C58H66N10O9 • C23H16O6 and the molecular weight is 1435.58 g/mol.

The structural formula is:

The drug product consists of pasireotide pamoate uniformly distributed within microspheres which are made of biodegradable copolymers of poly (D,L-lactide-co-glycolide) acids (PLGA).

SIGNIFOR LAR is available in a vial containing the sterile pasireotide pamoate, PLGA microspheres powder, 10 mg, 20 mg, 30 mg, 40 mg, and 60 mg to be reconstituted with the provided 2 mL sterile diluent.

Each vial contains:

 | 10 mg | 20 mg | 30 mg | 40 mg | 60 mg
Pasireotide pamoate | 13.71 mg* | 27.42 mg* | 41.13 mg* | 54.84 mg* | 82.26 mg*
Poly(D,L-lactide-co-glycolide) [50-60:40-50] | 13.15 mg | 26.29 mg | 39.44 mg | 52.58 mg | 78.87 mg
Poly(D,L-lactide-co-glycolide) [50:50] | 13.15 mg | 26.29 mg | 39.44 mg | 52.58 mg | 78.87 mg
*corresponds to 10 mg, 20 mg, 30 mg, 40 mg, and 60 mg of pasireotide base, respectively.

Each diluent prefilled syringe contains:

Mannitol | 90 mg
Carboxymethylcellulose sodium | 14 mg
Poloxamer 188 | 4 mg
Water for injections | add to 2 mL

12 CLINICAL PHARMACOLOGY

12.1 Mechanism of Action

SIGNIFOR LAR is an injectable cyclohexapeptide, somatostatin analog. Pasireotide exerts its pharmacological activity via binding to somatostatin receptors (SSTR). There are 5 known human somatostatin receptor subtypes: SSTR 1, 2, 3, 4, and 5. These receptor subtypes are expressed in different tissues under normal physiological conditions. Somatostatin analogs bind to SSTRs with different potencies. Pasireotide binds with high affinity to 4 of the 5 SSTRs (see Table 4).

Table 4 – Binding Affinities of Somatostatin (SRIF-14) and Pasireotide to the Five Human SSTR Subtypes (SSTR 1-5)
Compound | SSTR1 | SSTR2 | SSTR3 | SSTR4 | SSTR5
Somatostatin (SRIF-14) | 0.93 ± 0.12 | 0.15 ± 0.02 | 0.56 ± 0.17 | 1.5 ± 0.4 | 0.29 ± 0.04
Pasireotide | 9.3 ± 0.1 | 1.0 ± 0.1 | 1.5 ± 0.3 | > 100 | 0.16 ± 0.01
Results are the mean + SEM of IC50 values expressed as nmol/l (nM).

12.2 Pharmacodynamics

Somatostatin receptors are expressed in many tissues including neuroendocrine tumors (e.g., growth hormone or adrenocorticotropic hormone secreting pituitary adenomas).

Acromegaly

Pasireotide binds to SSTR2 and SSTR5 subtype receptors which may be relevant for inhibition of GH secretion. In vivo studies show that SIGNIFOR LAR lowers GH and IGF-1 levels in patients with acromegaly.

Cushing's Disease

Corticotroph tumor cells from Cushing's disease patients frequently over-express SSTR5 whereas the other receptor subtypes are often not expressed or are expressed at lower levels. Pasireotide binds and activates the SSTRs resulting in inhibition of ACTH secretion, which leads to decreased cortisol secretion.

Cardiac Electrophysiology

Individually corrected QT (QTcI) interval was evaluated in a randomized, blinded, crossover study in healthy subjects investigating pasireotide subcutaneous doses of 0.6 mg and 1.95 mg twice daily, respectively. The maximum mean (95% upper confidence bound) placebo-subtracted QTcI change from baseline was 12.7 (14.7) ms and 16.6 (18.6) ms, respectively. Both pasireotide doses decreased heart rate, with a maximum mean (95% lower confidence bound) placebo-subtracted change from baseline of -10.9 (-11.9) beats per minute (bpm) observed at 1.5 hours for pasireotide 0.6 mg twice daily, and -15.2 (-16.5) bpm at 0.5 hours for pasireotide 1.95 mg twice daily.

The predicted pasireotide peak concentration (25.8 ng/mL) following SIGNIFOR LAR 60-mg dose in acromegaly patients is similar to the observed peak concentration (24.3 mg/mL) of the subcutaneous SIGNIFOR 0.6 mg twice daily dose and below the observed peak concentration (80.6 ng/mL) of the subcutaneous SIGNIFOR 1.95 mg twice daily dose. The predicted pasireotide peak concentration for the SIGNIFOR LAR dose of 40 mg in Cushing's disease patients is 14 ng/mL.

12.3 Pharmacokinetics

Pasireotide for intramuscular use is formulated as microspheres for long-acting release. After a single injection, the plasma pasireotide concentration shows an initial burst release on the injection day, followed by a dip from Day 2 to Day 7, then a slow increase to the maximum concentration around Day 21, and a slow declining phase over the next weeks, concomitant with the terminal degradation phase of the polymer matrix of the dosage form.

Absorption and Distribution

No studies have been conducted to evaluate the absolute bioavailability of pasireotide in humans. Food effect is unlikely to occur since SIGNIFOR LAR is administered via a parenteral route.

In healthy volunteers, pasireotide administered as SIGNIFOR LAR is widely distributed with large apparent volume of distribution (Vz/F > 100 L). Distribution between blood and plasma is concentration-independent and shows that pasireotide is primarily located in the plasma (91%). Plasma protein binding is moderate (88%) and independent of concentration.

Pasireotide has low passive permeability and is likely to be a substrate of P-glycoprotein (P-gp), but the impact of P-gp on the ADME (absorption, distribution, metabolism, excretion) of pasireotide is expected to be low. In clinical testing in healthy volunteers, P-gp inhibition did not affect the rate or extent of pasireotide availability [see Drug Interactions (7.1)]. At therapeutic dose levels, pasireotide is not expected to be a substrate of BCRP (breast cancer resistance protein), OCT1 (organic cation transporter 1), or OATP (organic anion-transporting polypeptides) 1B1, 1B3, or 2B1.

Elimination

Metabolism and Excretion

Pasireotide was shown to be highly metabolically stable in human liver and kidney microsomes. In healthy volunteers, pasireotide in its unchanged form is the predominant form found in plasma, urine and feces. Somatropin may increase CYP450 enzymes and, therefore, suppression of GH secretion by somatostatin analogs including pasireotide may decrease the metabolic clearance of compounds metabolized by CYP450 enzymes.

Pasireotide is eliminated mainly via hepatic clearance (biliary excretion) with a small contribution of the renal route. In a human ADME study with subcutaneous SIGNIFOR with a single dose 0.6 mg, 55.9 ± 6.63% of the radioactivity dose was recovered over the first 10 days post dosing, including 48.3 ± 8.16% of the radioactivity in feces and 7.63 ± 2.03% in urine.

The apparent clearance (CL/F) of SIGNIFOR LAR in healthy volunteers is on average 4.5-8.5 L/hour.

Steady-State Pharmacokinetics

PK steady-state for SIGNIFOR LAR is achieved after 3 monthly doses. Following multiple intramuscular doses every 4 weeks (every 28 days), SIGNIFOR LAR demonstrates approximately dose-proportional PK exposures (steady-state trough; Ctrough, ss) in the dose range of 10 mg to 60 mg every 4 weeks.

Special Populations

Population PK analyses of SIGNIFOR LAR suggest that race, gender, and body weight do not have clinically relevant influence on circulating levels of pasireotide. No dose adjustment is required for demographics.

Pediatric Patients

No studies have been performed in pediatric patients [see Use in Specific Populations (8.4)].

Geriatric Patients

Age is not a significant covariate in the population PK analysis. Therefore age is not expected to significantly impact circulating levels of pasireotide.

Efficacy and safety data on patients older than 65 years are limited [see Use in Specific Populations (8.5)].

Hepatic Impairment

In a clinical study with a single subcutaneous dose of 600 µg pasireotide in subjects with impaired hepatic function (Child-Pugh A, B, and C), subjects with moderate and severe hepatic impairment (Child-Pugh B and C) showed significantly higher exposures than subjects with normal hepatic function. Upon comparing with the control group, AUCinf was increased by 12%, 56%, and 42%; and Cmax was increased by 3%, 46%, and 33% respectively, in the mild, moderate, and severe hepatic impairment groups [see Use in Specific Populations (8.6), Dosage and Administration (2.5)].

Renal Impairment

Clinical studies have not been performed in patients with renal impairment. However, renal clearance has a minor contribution to the elimination of pasireotide in humans. Renal function (creatinine clearance and estimated glomerular filtration rate) is not a covariate in the population PK analysis. Therefore, renal function is not expected to significantly impact the circulating levels of pasireotide [see Use in Specific Populations (8.7)].

13 NONCLINICAL TOXICOLOGY

13.1 Carcinogenesis, Mutagenesis, Impairment of Fertility

Carcinogenesis

A lifetime carcinogenicity study was conducted in rats and transgenic mice. Rats were given daily subcutaneous doses of pasireotide at 0.01 mg/kg/day, 0.05 mg/kg/day, and 0.3 mg/kg/day for 104 weeks. There were no drug-related tumors in rats at exposures up to 5-times higher than the maximum recommended clinical exposure of the pasireotide LAR 60 mg dose. Mice were given subcutaneous doses of pasireotide at 0.5 mg/kg/day, 1 mg/kg/day, and 2.5 mg/kg/day for 26 weeks and did not identify any carcinogenic potential.

Mutagenesis

Pasireotide was not genotoxic in a battery of in vitro assays (Ames mutation test in Salmonella and Escherichia coli and mutation test in human peripheral lymphocytes). Pasireotide was not genotoxic in an in vivo rat bone marrow nucleus test.

Impairment of Fertility

Subcutaneous dosing at 0.1 mg/kg/day before mating and continuing into gestation in rats at exposures less than the human clinical exposure based on body surface area comparisons across species resulted in statistically significant increased implantation loss and decreased viable fetuses, corpora lutea, and implantation sites. Abnormal cycles or acyclicity were observed at 1 mg/kg/day (4-fold higher than the maximum therapeutic exposure of pasireotide LAR based on surface area, comparisons across species).

14 CLINICAL STUDIES

14.1 Drug-Naïve Patients with Acromegaly

A multicenter, randomized, double-blind study was conducted to assess the safety and efficacy of SIGNIFOR LAR in patients with active acromegaly. A total of 358 patients naïve to drugs used to treat acromegaly were randomized in a 1:1 ratio to SIGNIFOR LAR or another somatostatin analog active comparator. Randomization was stratified based on previous pituitary surgical status (e.g., at least 1 prior pituitary surgery versus no prior pituitary surgery).

In the overall study population, 52% were female and the average age of patients was 45 years. Sixty percent of patients were Caucasian, 23% Asian, 12% Other, 3% American Indian, and 2% were Black. Forty-two percent of patients had previous pituitary surgery, and 1 patient had a history of pituitary radiation therapy. Median time between diagnosis and trial participation was 6 months. Median GH was 8.8 mcg/L (range: 0.8-200 mcg/L) and 10.1 mcg/L (range: 0.6-169.6 mcg/L) for SIGNIFOR LAR and active comparator, respectively at baseline. Median standardized IGF-1, defined as IGF-1 value divided by the ULN (i.e., fold above the ULN), was 2.9 (range: 0.9-6.9) and 2.9 (range: 0.8-7.3), for SIGNIFOR LAR and active comparator, respectively, at baseline.

The starting dose of SIGNIFOR LAR was 40 mg. Dose increase was allowed in both arms, at the discretion of investigators, after 3 and 6 months of treatment if mean GH was greater than or equal to 2.5 mcg/L and/or IGF-1 was greater than the ULN for age and sex. The maximum allowed dose for SIGNIFOR LAR was 60 mg. The maximum dose of the active comparator was not used in this trial because the trial was multi-national and the maximum dose approved in the US was not approved in all participating countries.

The efficacy endpoint was the proportion of patients with a mean GH level less than 2.5 mcg/L and a normal IGF-1 levels at month 12 (age- and sex-adjusted) (see Table 5, Figure 3, and Figure 4). The proportion of patients achieving this level of control was 31.3% and 19.2% for SIGNIFOR LAR and active comparator, respectively. The changes in mean GH and IGF-1 levels by study visits in subjects with a measurement at these visits (observed cases) are shown in Figures 3 and 4.

Table 5 – Results at Month 12 in Drug-Naïve Patients Study
 | SIGNIFOR LAR; (40-60 mg); %; N = 176 | Active Comparatorc; %; N = 182
GH < 2.5 mcg/L and normalized IGF-1a | 31.3%b | 19.2%
GH < 2.5 mcg/L and IGF-1 ≤ ULN | 35.8% | 20.9%
Normalized IGF-1 | 38.6%b | 23.6%
GH < 2.5 mcg/L | 48.3% | 51.6%
aPrimary endpoint [patients with IGF-1< lower limit of normal (LLN) were not considered as "responders"].
ULN = Upper limit of normal.
bp-value < 0.01 for treatment difference.
cThe maximum dose approved for use in the United States was not used in this trial but the majority of patients were receiving the dose most commonly used in the United States to treat acromegaly.

Figure 3. Mean GH (mcg/L) Levels By Visit in Drug Naïve Patient Study [Numbers of patients with a GH value at the given timepoint for SIGNIFOR LAR/Active comparator arm are displayed as xxx/xxx on the x-axis.]

Figure 4. Mean Standardized IGF-1 Levels [Fold above the upper limit of normal for the assay] By Visit in Drug Naïve Patient Study [Numbers of patients with an IGF-1 value at the given timepoint for SIGNIFOR LAR/Active comparator arm are displayed as xxx/xxx on the x axis.]

Biochemical control was achieved by Month 3 in 30.1% of patients in the SIGNIFOR LAR arm. Ninety-eight percent of patients treated with SIGNIFOR LAR had either a reduction or no change in tumor volume from baseline assessed by MRI at Month 12. The median (range) change in tumor volume was a reduction of 39.8% (-97.6% to 16.9%).

Additionally, ring size and acromegaly symptoms score (i.e., headache, fatigue, perspiration, paresthesia, and osteoarthralgia) were followed. At Month 12, reductions in ring size and in symptom severity scores in both treatment groups compared to baseline were noted.

14.2 Patients with Acromegaly Inadequately Controlled on Other Somatostatin Analogs

A multicenter, randomized, 3-arm study was conducted in patients with acromegaly inadequately controlled on somatostatin analogs. Patients were randomized to double-blind SIGNIFOR LAR 40 mg (n = 65) or SIGNIFOR LAR 60 mg (n = 65) or to continued open-label pretrial somatostatin analog therapies at maximal or near maximal doses (n = 68). A total of 181 patients completed the 6-month trial.

Inadequate control was defined as a GH concentration of greater than 2.5 mcg/L (i.e., mean of 5 samples over 2 hours) and a sex- and age-adjusted IGF-1 level greater than 1.3 times the upper limit of normal. Patients were required to have been treated with other somatostatin analogs for at least 6 months prior to randomization. Note that the maximum dose for one of the active comparators approved for use in the United States was not used in this multinational trial; approximately 75% of the population in the comparator group was receiving this active comparator.

In the overall study population, 56% were female and the average age of patients was 45 years. Eighty-one percent of patients were Caucasian, 7% Other, 8% Black, 2% American Indian, and 2% Asian. The percentage of patients with previous pituitary surgery in the SIGNIFOR LAR 40 mg and 60 mg arms, and in the active control arm was 77%, 63%, and 60%, respectively. Three percent of patients in the SIGNIFOR LAR groups and 7% of patients in the active control arm had prior radiation therapy. Median (range) time from diagnosis to participation in this trial was 50 (10-337) months, 55 (8-357) months, and 54 (8-357) months in the SIGNIFOR LAR 40 mg, 60 mg and the pretrial therapy arms, respectively. At baseline, median (range) GH was 7.1 (1.0-200) mcg/L, 5.3 (1.4-113.8) mcg/L and 6.1 (1.0-92.4) mcg/L in the SIGNIFOR LAR 40 mg, 60 mg and the pretrial therapy arms, respectively. Baseline median standardized IGF-1 (defined as IGF-1 value divided by the ULN) values were 2.3, 2.6 and 2.9 in the SIGNIFOR LAR 40 mg, 60 mg and the pretrial therapy arms, respectively.

The efficacy endpoint was the proportion of patients with a mean GH level less than 2.5 mcg/L and normal IGF-1 levels at week 24. The primary analysis compared SIGNIFOR LAR 60 mg and 40 mg to continued pretrial therapy (i.e., no change in treatment). The proportion of patients achieving biochemical control was 15.4% and 20.0% for SIGNIFOR LAR 40 mg and 60 mg, respectively, at 6 months.

Biochemical control was achieved by Month 3 in 15.4% and 18.5% of patients in the SIGNIFOR LAR 40 mg and 60 mg arms, respectively.

Table 6 – Results at 6 Months in Inadequately Controlled Patient Study
 | SIGNIFOR LAR 40 mg % N = 65 | SIGNIFOR LAR 60 mg % N = 65 | Continued Pre-Trial Therapy Control Armb % N = 68
GH < 2.5 mcg/L and normalized IGF-1a | 15.4% | 20.0% | 0%
Normalization of IGF-1 | 24.6% | 26.2% | 0%
GH < 2.5 mcg/L | 35.4% | 43.1% | 13.2%
aPrimary endpoint (patients with IGF-1 < lower limit of normal (LLN) were not considered as "responders").
bFor one of the active comparators, the maximum dose approved for use in the United States was not used in this trial but the majority of patients were receiving the dose most commonly used in the United States to treat acromegaly.

Eighty-one percent and 70% of patients treated with SIGNIFOR LAR 40 mg and 60 mg, respectively, had either a reduction or no change in tumor volume from baseline assessed by MRI at Month 6. The median (range) change in tumor volume was a reduction of -10.4% (-74.5% to 19.4%) and -6.3% (-66.7% to 14.5%) from baseline for SIGNIFOR LAR 40 mg and 60 mg, respectively.

14.3 Patients with Cushing's Disease

A Phase 3, randomized, double-blind, multicenter study was conducted to evaluate the safety and efficacy of two dose regimens of SIGNIFOR LAR over a 12-month treatment period in patients with persistent or recurrent Cushing's disease, or de novo patients who were not considered candidates for pituitary surgery.

The study enrolled 150 patients with a screening mean urinary free cortisol level (mUFC) ≥ 1.5 and ≤ 5 x ULN, who were randomized in a 1:1 ratio to receive a SIGNIFOR LAR starting dose of either 10 mg intramuscularly once every 28 days or 30 mg intramuscularly once every 28 days. Randomization was stratified by values of mUFC at screening (1.5 to < 2 x ULN versus 2 to 5 x ULN, respectively).

After four months of treatment, patients who had a mUFC ≤ 1.5 x ULN continued on the blinded dose to which they were randomized. Patients with a mUFC > 1.5 x ULN at Month 4 had their doses increased in a blinded manner from 10 mg to 30 mg, or from 30 mg to 40 mg, provided there were no tolerability concerns. Additional dose increases were allowed at Month 7 and Month 9 (by one dose level if the mUFC was > 1 x ULN).

Dose reduction by one dose level for tolerability was allowed in a blinded fashion for the first seven months, with a minimum dose level of 5 mg. After the first seven months, blinded down titration of more than one dose level was allowed at any month.

After twelve months of treatment (core phase), patients had the option to enter an extension to continue to receive SIGNIFOR LAR if they benefited from treatment.

The primary efficacy endpoint was the proportion of patients in each arm who were mUFC responders (mUFC ≤ ULN) after seven months of treatment, with or without up-titration at Month 4. The key secondary endpoint was the proportion of patients in each arm who were mUFC responders after seven months of treatment and who did not up-titrate the dose prior to Month 7. The pre-specified boundary of the lower limit of the 95% confidence interval (CI) for efficacy for both the primary and key secondary endpoints was 15%. Patients with missing mUFC assessment at Month 7 were classified as non-responders. Other secondary endpoints included changes from baseline in 24-hour UFC, plasma ACTH, and serum cortisol levels. All analyses were conducted based on the randomized dose groups.

Baseline demographics and disease history were well balanced between the two randomized dose groups and consistent with the epidemiology of the disease. The mean age of patients was approximately 38.5 years with a predominance of female patients (78.7%). The majority of the patients had persistent or recurrent Cushing's disease (82.0%). The median value of the baseline 24-hour mUFC for all patients was 396.9 nmol/24 hours (ULN: 166.5 nmol/24 hours). About three-quarters of all randomized patients completed seven months of treatment, and about two-thirds of all randomized patients completed twelve months of treatment.

The study met the primary efficacy objective for both dose groups. Patients were considered responders if they remained on treatment until at least Month 7 and achieved a Month 7 mUFC ≤ 1 x ULN, regardless of up-titration at Month 4. The proportion of patients with mUFC response at Month 7 was 39.2% (95% CI: 28.0, 51.2) in the 10 mg arm and 40.8% (95% CI: 29.7, 52.7) in the 30 mg arm. The responder rate at Month 12 was 35.1% (26/74) and 25.0% (19/76) in the 10 mg and 30 mg starting dose groups, respectively.

Table 7 – Response Rates at Month 7 per Randomized Dose Group and According to Screening mUFC
 | Pasireotide LAR 10 mg Every 28 Days | Pasireotide LAR 30 mg Every 28 Days
Screening mUFC category | n/N (%) 95% CI | n/N (%) 95% CI
All patients | 29/74 (39.2) (28.0, 51.2) | 31/76 (40.8) (29.7, 52.7)
≥ 1.5 x ULN to < 2 x ULN | 11/25 (44.0) (24.4, 65.1) | 13/25 (52.0) (31.3, 72.2)
≥ 2 x ULN to ≤ 5 x ULN | 18/49 (36.7) (23.4, 51.7) | 18/51 (35.3) (22.4, 49.9)
There were 17 (23.0%) patients in 10 mg arm and 9 (11.8%) in the 30 mg arm with missing value mUFC assessments at Month 7 who were classified as non-responders.

The study met the key secondary efficacy objective for both dose groups. At Month 4, 31/74 (41.9%) and 28/76 (36.8%) patients were up-titrated in the pasireotide LAR 10 mg and 30 mg arms, respectively. When all patients who up-titrated prior to Month 7 were counted as non-responders, Month 7 mUFC response was observed in 25.7% (95% CI: 16.2 to 37.2) and 31.6% (95% CI: 21.4 to 43.3) of patients randomized to pasireotide LAR at a starting dose of 10 mg once every 28 days and 30 mg once every 28 days, respectively.

A secondary efficacy analysis was conducted for the combined proportion of patients who attained mUFC ≤ ULN (controlled) or had at least 50% reduction in mUFC (partially controlled) in the core phase of the study. The combined rate of controlled or partially controlled responders at Month 7 constituted 44.6% and 53.9% of patients randomized to the 10 mg and 30 mg dose groups, respectively (Table 8).

Table 8 – Response Rates at Month 7 per Randomized Dose Group - Supportive Efficacy Analysis
Response Category | Pasireotide LAR 10 mg Every 28 Days (N = 74) n (%) | Pasireotide LAR 30 mg Every 28 Days (N = 76) n (%)
Controlled (mUFC ≤ ULN) | 29 (39.2%) | 31 (40.8%)
Partially controlled (≥ 50% reduction in mUFC) | 4 (5.4%) | 10 (13.2%)
Combined | 33 (44.6%) | 41 (53.9%)

Decreases in median mUFC levels at Month 7 compared to baseline, as measured by overall percentage of reduction, are shown in Table 9. Reductions in serum cortisol and plasma ACTH levels were also observed at Months 7 and 12 for each dose group.

Table 9 – Median Percentage Change from Baseline in Mean Urinary Free Cortisol (mUFC) at Month 7 by Randomized Dose Group
 |  | Pasireotide LAR 10 mg Every 28 Days % change | Pasireotide LAR 30 mg Every 28 Days % change
mUFC levels (nmol/24hr) Baseline | N Mean (SD) Median | 74 462.6 (256.41) 409.8 | 76 477.1 (331.75) 371.6
Median change in mUFC (% from baseline) | Month 7 | -41.3% | -41.4%
Note: Median % change from baseline in mUFC at Month 7 are calculated by imputing missing values with the worst observed % change in mUFC at Month 7 within each treatment group.

16 HOW SUPPLIED/STORAGE AND HANDLING

16.1 How Supplied

SIGNIFOR LAR for injectable suspension is supplied in a single-use kit containing the following:

- One 6-mL brownish glass vial with a grey rubber stopper of SIGNIFOR LAR containing slightly yellow to yellow powder with a flip-off cap
- One 3-mL glass barrel/grey rubber stopper prefilled syringe containing 2 mL of clear, colorless to slightly yellow/brown diluent solution for reconstitution
- One sterile 20G x 1.5" stainless steel, polypropylene safety injection needle
- One vial adapter made of polycarbonate for drug product reconstitution

SIGNIFOR LAR kits are available in the following strengths:

SIGNIFOR LAR Kit | Final Concentration When Reconstituted (total product strength per total volume) | Final Concentration When Reconstituted (per mL) | Flip-off Cap Color | NDC
10 mg | 10 mg/2 mL | 5 mg/mL | Brown | 55292-139-01
20 mg | 20 mg/2 mL | 10 mg/mL | Gray | 55292-140-01
30 mg | 30 mg/2 mL | 15 mg/mL | Lilac | 55292-141-01
40 mg | 40 mg/2 mL | 20 mg/mL | Red | 55292-142-01
60 mg | 60 mg/2 mL | 30 mg/mL | Orange | 55292-143-01

16.2 Storage and Handling

Store at 2°C to 8°C (36°F-46°F). Do not freeze.

SIGNIFOR LAR should be stored at refrigerated temperatures between 2°C to 8°C (36°F-46°F) until the time of use. SIGNIFOR LAR drug product kit should remain at room temperature for a minimum of 30 minutes before reconstitution, but should not exceed 24 hours at room temperature. However, after preparation of the drug suspension, it must be administered immediately.

17 PATIENT COUNSELING INFORMATION

Advise the patient to read the FDA-approved patient labeling (Patient Information).

- Instruct patients on the importance of adhering to their return visit schedule.
- Advise patients that SIGNIFOR LAR should only be administered by a trained healthcare professional.

Hyperglycemia, Diabetes, and Ketoacidosis

- Advise patients to assess FPG and HbA1c prior to starting treatment with SIGNIFOR LAR and advise patients to consistently monitor blood glucose levels, particularly after the start of treatment or after dose changes, so that appropriate action can be taken. Advise patients to contact their healthcare provider if they experience signs or symptoms of diabetes or ketoacidosis [see Warnings and Precautions (5.1)].

Bradycardia and QT Prolongation

- Advise patients that an ECG will be taken before treatment and periodically thereafter. Advise patients with cardiac disease and with risk factors for QT prolongation and bradycardia that adjustments in cardiac medications may be made and electrolyte disturbances may require correction [see Warnings and Precautions (5.2)].

Liver Test Elevations

- Advise patients that liver function will be assessed prior to starting treatment with SIGNIFOR LAR and will be closely monitored for the first three months of treatment and thereafter as clinically indicated [see Warnings and Precautions (5.3)].

Cholelithiasis and Complications of Cholelithiasis

- Inform patients that cholelithiasis and complications of cholelithiasis have been reported with the use of SIGNIFOR LAR [see Warnings and Precautions (5.4)].
- Advise patients to contact their healthcare provider if they experience signs or symptoms of gallstones (cholelithiasis) or complications of cholelithiasis (e.g., cholecystitis or cholangitis) [see Warnings and Precautions (5.4)].
- Advise patients that the gallbladder will be monitored by ultrasound periodically [see Warnings and Precautions (5.4)].

Pituitary Hormone Deficiency(ies)

- Advise patients that monitoring of anterior pituitary function will be performed periodically [see Warnings and Precautions (5.5)].

Steatorrhea and Malabsorption of Dietary Fats

- Advise patients to contact their healthcare provider if they experience new or worsening symptoms of steatorrhea, stool discoloration, loose stools, abdominal bloating, and weight loss [see Warnings and Precautions (5.6)].

Manufactured for:
Recordati Rare Diseases Inc.,
Bridgewater, NJ 08807 U.S.A

Patient Information
SIGNIFOR® LAR (sig-na-for L.A.R.)
(pasireotide)
for injectable suspension, for intramuscular use

Read this Patient Information before you start receiving SIGNIFOR LAR, and each time you receive it. There may be new information. This leaflet does not take the place of talking to your healthcare provider about your medical condition or your treatment.

What is SIGNIFOR LAR?

SIGNIFOR LAR is a prescription medicine used to treat people with:

- acromegaly for whom surgery has not worked well enough or who cannot have surgery.
- Cushing's disease for whom surgery has not worked well enough or who cannot have surgery.

It is not known if SIGNIFOR LAR is safe and effective for use in children.

What should I tell my healthcare provider before receiving SIGNIFOR LAR?

Before you receive SIGNIFOR LAR, tell your healthcare provider about all of your medical conditions, including if you:

- have high blood sugar (hyperglycemia).
- have diabetes.
- have or have had heart problems, including an abnormal heart rate or rhythm or problems with the electrical system of your heart (QT prolongation).
- have a low level of potassium or magnesium in your blood.
- have liver problems.
- have gallstones (cholelithiasis).
- are pregnant or plan to become pregnant. It is not known if SIGNIFOR LAR will harm your unborn baby.
- are breastfeeding or plan to breastfeed. It is not known if SIGINFOR LAR passes into your breast milk. Talk to your healthcare provider about the best way to feed your baby if you take SIGNIFOR LAR.

Treatment with SIGNIFOR LAR may result in improved fertility and the possibility of unplanned pregnancy in females who have acromegaly or Cushing's disease and have not gone through menopause. Talk to your healthcare provider about birth control methods that may be right for you during treatment with SIGNIFOR LAR.

Tell your healthcare provider about all the medicines you take, including prescription and over-the-counter medicines, vitamins, and herbal supplements.
SIGNIFOR LAR and other medicines may affect each other, causing side effects. SIGNIFOR LAR may affect the way other medicines work, and other medicines may affect how SIGNIFOR LAR works. Your healthcare provider may need to change your dose of SIGNIFOR LAR or your other medicines. Especially tell your healthcare provider if you take:

- medicines to control your heart beat (antiarrhythmics)
- medicines to control your blood pressure (such as beta-blockers or calcium channel blockers)
- medicines to control the potassium and magnesium (electrolytes) levels in your body
- medicines that may affect the way the electrical system of your heart works (QT prolongation)
- cyclosporine
- bromocriptine

Ask your healthcare provider for a list of these medicines if you are not sure.
Know the medicines you take. Keep a list of them to show to your healthcare provider and pharmacist when you get a new medicine.

How will I receive SIGNIFOR LAR?

- SIGNIFOR LAR must be given by a trained healthcare provider as an injection into the muscle of your buttocks (intramuscularly).
- Your healthcare provider will tell you how much SIGNIFOR LAR you will receive and when you will receive it.
- Your healthcare provider may change your dose of SIGNIFOR LAR or the length of time between your injections. Your healthcare provider will tell you how long you need to receive SIGNIFOR LAR.
- Before you receive SIGNIFOR LAR for the first time, your healthcare provider should do a blood test to check your fasting blood sugar level, hemoglobin A1c level, electrolyte levels, and your liver function.
- You will need to check your blood sugar levels during treatment with SIGNIFOR LAR, especially after you start treatment with SIGNIFOR LAR and after your dose is increased. Your healthcare provider will tell you how often you should check your blood sugar levels.
- Before you receive SIGNIFOR LAR for the first time and during your treatment, your healthcare provider should do a test to check your heart (electrocardiogram).
- If you miss a dose of SIGNIFOR LAR, you may receive your missed dose up to 14 days before your next dose.
- It is important that you keep your scheduled appointments with your healthcare provider during treatment with SIGNIFOR LAR.

What are the possible side effects of SIGNIFOR LAR?

SIGNIFOR LAR may cause serious side effects, including:

- high blood sugar (hyperglycemia), diabetes, and increased ketones in your urine or blood (ketoacidosis). High blood sugar and diabetes are serious but common side effects of SIGNIFOR LAR. Ketoacidosis is a serious condition that should be evaluated and treated promptly.Your healthcare provider should check your blood sugar level before you start receiving SIGNIFOR LAR and while you receive it. Tell your healthcare provider right away if you have any of these symptoms:

o feel very thirsty
o urinate more than usual

o nausea
o vomiting
o abdominal pain

o increased appetite with weight loss
o tiredness

o fruity scented breath
o trouble breathing

o confusion

If you get hyperglycemia while receiving SIGNIFOR LAR, your healthcare provider may give you another medicine to lower your blood sugar. Your healthcare provider may also change your dose of SIGNIFOR LAR or advise you to stop receiving it.

- slow heart rate (bradycardia). SIGNIFOR LAR can cause your heart to beat slower. People who have, or have had heart problems, or take certain medicines used to treat slow heart rate or that may cause a slow heart rate, are at higher risk for bradycardia. Tell your healthcare provider if you get any of these symptoms:

o weakness
o dizziness

o fainting or near fainting spells

- changes in the electrical system of your heart (QT interval prolongation). Tell your healthcare provider if you get any of these symptoms:

o weakness
o dizziness

o fainting or near fainting spells

- higher than normal liver function tests. Your healthcare provider should do blood tests to check your liver while you receive SIGNIFOR LAR.
- gallstones (cholelithiasis) and complications that can happen if you have gallstones. Gallstones are a serious but common side effect of SIGNIFOR LAR. Possible complications of gallstones include inflammation and infection of the gall bladder. Your healthcare provider should do a test (ultrasound) to check your gall bladder before and during your treatment with SIGNIFOR LAR. Tell your healthcare provider if you get any of these symptoms:

o sudden pain in your upper right stomach area (abdomen)
o sudden pain in your right shoulder or between your shoulder blades

o yellowing of your skin and whites of your eyes
o fever with chills
o nausea

- low levels of pituitary hormones (pituitary insufficiency). SIGNIFOR LAR may reduce the pituitary hormones in your body. Your healthcare provider should do a blood test to check your pituitary hormone levels before you start receiving SIGNIFOR LAR and while you receive it. Tell your healthcare provider if you get any of these symptoms:

o nausea and vomiting
o tiredness
o dizziness
o diarrhea

o low blood sugar levels
o loss of appetite
o weight loss

- fatty stool. SIGNIFOR LAR may cause your body to have issues absorbing dietary fats. Tell your healthcare provider if you have any new or worsening symptoms including fatty stools, changes in the color of your stools, loose stools, stomach (abdominal) bloating or weight loss.

The most common side effects of SIGNIFOR LAR include:

• diarrhea
• headache
• stomach-area pain
• hair loss
• stuffy nose and sore throat
• low blood sugar
• limb swelling
• loss of appetite

• nausea
• increase in the level of an enzyme in your blood called creatine phosphokinase (CPK)
• tiredness
• stomach bloating
• high blood pressure
• back pain

Tell your healthcare provider if you have any side effect that bothers you or that does not go away.

These are not all the possible side effects of SIGNIFOR LAR. For more information, ask your healthcare provider or pharmacist.

Call your doctor for medical advice about side effects. You may report side effects to FDA at 1–800–FDA–1088.

How should I store SIGNIFOR LAR?

- Store SIGNIFOR LAR in the refrigerator between 36°F to 46°F (2°C to 8°C).
- Do not freeze SIGNIFOR LAR.
- Take SIGNIFOR LAR out of the refrigerator at least 30 minutes before you will receive it to allow it to come to room temperature.
- Do not use SIGNIFOR LAR if it has been out of the refrigerator and at room temperature for more than 24 hours.
- Your healthcare provider should give you SIGNIFOR LAR right away after it is mixed.

Keep SIGNIFOR LAR and all medicines out of the reach of children.

General information about the safe and effective use of SIGNIFOR LAR.

Medicines are sometimes prescribed for purposes other than those listed in a Patient Information leaflet. Do not use SIGNIFOR LAR for a condition for which it was not prescribed. Do not give SIGNIFOR LAR to other people, even if they have the same symptoms that you have. It may harm them.

This Patient Information leaflet summarizes the most important information about SIGNIFOR LAR. If you would like more information, talk to your healthcare provider. You can ask your pharmacist or healthcare provider for information about SIGNIFOR LAR that is written for health professionals.

For more information go to www.SIGNIFORLAR.com or call 1-888-575-8344.

What are the ingredients in SIGNIFOR LAR?

Active ingredient: pasireotide pamoate

Inactive ingredients:

Vial: Poly(D,L-lactide-co-glycolide)

Prefilled syringe: Mannitol, carboxymethylcellulose sodium, poloxamer 188, and water for injections

Manufactured for:
Recordati Rare Diseases Inc., Bridgewater, NJ 08807 U.S.A

This Patient Information has been approved by the U.S. Food and Drug Administration.

Revised: 7/2024

PRINCIPAL DISPLAY PANEL - Kit Carton - NDC 55292 139 01

NDC 55292 139 01

Signifor® LAR
(pasireotide)

For Injectable Suspension

For Intramuscular Use

Should only be administered by a trained health care professional.

Remove the injection kit from the refrigerator and let the kit stand at room
temperature for a minimum of 30 minutes before reconstitution,
but do not exceed 24 hours.

RECORDATI
RARE DISEASES
GROUP

Rx only

10 mg

Each carton contains:

- One vial containing Signifor® LAR powder
- One prefilled syringe containing diluent
  solution for reconstitution
- One vial adapter for drug product reconstitution
- One 20G x 1.5" safety injection needle

PRINCIPAL DISPLAY PANEL - Kit Carton - NDC 55292 140 01

NDC 55292 140 01

Signifor® LAR
(pasireotide)

For Injectable Suspension

For Intramuscular Use

Should only be administered by a trained health care professional.

Remove the injection kit from the refrigerator and let the kit stand at room
temperature for a minimum of 30 minutes before reconstitution,
but do not exceed 24 hours.

RECORDATI
RARE DISEASES
GROUP

Rx only

20 mg

Each carton contains:

- One vial containing Signifor® LAR powder
- One prefilled syringe containing diluent
  solution for reconstitution
- One vial adapter for drug product reconstitution
- One 20G x 1.5" safety injection needle

PRINCIPAL DISPLAY PANEL - Kit Carton - NDC 55292 141 01

NDC 55292 141 01

Signifor® LAR
(pasireotide)

For Injectable Suspension

For Intramuscular Use

Should only be administered by a trained health care professional.

Remove the injection kit from the refrigerator and let the kit stand at room
temperature for a minimum of 30 minutes before reconstitution,
but do not exceed 24 hours.

RECORDATI
RARE DISEASES
GROUP

Rx only

30 mg

Each carton contains:

- One vial containing Signifor® LAR powder
- One prefilled syringe containing diluent
  solution for reconstitution
- One vial adapter for drug product reconstitution
- One 20G x 1.5" safety injection needle

PRINCIPAL DISPLAY PANEL - Kit Carton - NDC 55292 142 01

NDC 55292 142 01

Signifor® LAR
(pasireotide)

For Injectable Suspension

For Intramuscular Use

Should only be administered by a trained health care professional.

Remove the injection kit from the refrigerator and let the kit stand at room
temperature for a minimum of 30 minutes before reconstitution,
but do not exceed 24 hours.

RECORDATI
RARE DISEASES
GROUP

Rx only

40 mg

Each carton contains:

- One vial containing Signifor® LAR powder
- One prefilled syringe containing diluent
  solution for reconstitution
- One vial adapter for drug product reconstitution
- One 20G x 1.5" safety injection needle

PRINCIPAL DISPLAY PANEL - Kit Carton - NDC 55292 143 01

NDC 55292 143 01

Signifor® LAR
(pasireotide)

For Injectable Suspension

For Intramuscular Use

Should only be administered by a trained health care professional.

Remove the injection kit from the refrigerator and let the kit stand at room
temperature for a minimum of 30 minutes before reconstitution,
but do not exceed 24 hours.

RECORDATI
RARE DISEASES
GROUP

Rx only

60 mg

Each carton contains:

- One vial containing Signifor® LAR powder
- One prefilled syringe containing diluent
  solution for reconstitution
- One vial adapter for drug product reconstitution
- One 20G x 1.5" safety injection needle